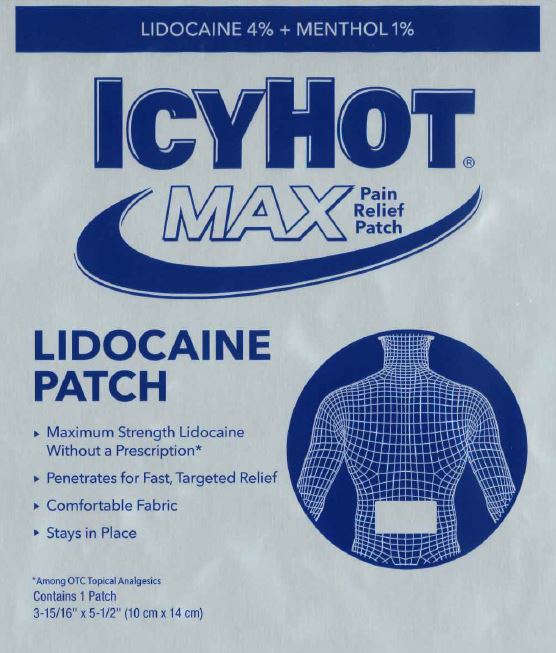 DRUG LABEL: Icy Hot
NDC: 62168-1720 | Form: PATCH
Manufacturer: Lead Chemical Co. Ltd.
Category: otc | Type: HUMAN OTC DRUG LABEL
Date: 20240102

ACTIVE INGREDIENTS: LIDOCAINE 240 mg/1 1; MENTHOL, UNSPECIFIED FORM 60 mg/1 1
INACTIVE INGREDIENTS: DIHYDROXYALUMINUM AMINOACETATE ANHYDROUS; ALUMINUM HYDROXIDE; CARBOXYMETHYLCELLULOSE SODIUM, UNSPECIFIED FORM; GLYCERIN; METHYLPARABEN; NONOXYNOL-30; POLYSORBATE 80; PROPYLENE GLYCOL; SILICON DIOXIDE; TARTARIC ACID; TITANIUM DIOXIDE; UREA; WATER

Icy Hot Max Pain Relief Patch

Active ingredients

Lidocaine 4%
Menthol 1%

Purposes

Topical anesthetic
Topical analgesic

Use

for the temporary relief of pain

Warnings

For external use only

Do not use

- on puncture wounds, cuts, irritated, damaged or swollen skin
- more than 1 patch on your body at a time or with other topical analgesics at the same time
- with a heating pad or apply local heat to the area of use

When using this product

- use only as directed
- do not bandage tightly
- avoid contact with the eyes and mucous membranes
- rare cases of serious burns have been reported with products of this type
- a transient burning sensation may occur upon application but generally disappears in several days
- dispose of used patch in manner that always keeps product away from children and pets. Used patches still contain the drug product that can produce serious adverse effects if a child or pet chews or ingests this patch.

Stop use and ask a doctor if

- condition worsens or symptoms persist for more than 7 days
- symptoms clear up and occur again within a few days
- severe burning sensation, redness, or irritation develops
- you experience signs of skin injury, such as pain, swelling, or blistering where the product was applied

If pregnant or breast-feeding,

ask a health professional before use.

Keep out of reach of children and pets.

If swallowed, get medical help or contact a Poison Control Center right away.

Directions

adults and children 12 years of age and older:

- clean and dry affected area
- remove backing from patch by firmly grasping both ends and gently pulling until backing separates in middle
- carefully remove smaller portion of backing from patch and apply exposed portion of patch to affected area
- once exposed portion of patch is positioned, carefully remove remaining backing to completely apply patch to affected area
- use 1 patch at a time and not more than 3 to 4 times daily

children under 12 years of age: consult a doctor

Inactive ingredients

aluminum glycinate, aluminum hydroxide, cellulose gum, glycerin, methyl acrylate/2-ethylhexyl acrylate copolymer, methylparaben, nonoxynol-30, polyacrylic acid, polysorbate 80, propylene glycol, silica, sodium polyacrylate, tartaric acid, titanium dioxide, urea, water

Package/Label Principal Display Panel

LIDOCAINE 4% + MENTHOL 1%

ICY HOT®
MAX
Pain Relief Patch

LIDOCAINE
PATCH

- Maximum Strength Lidocaine
  Without a Prescription*
- Penetrates for Fast, Targeted Relief
- Comfortable Fabric
- Stays in Place

*Among OTC Topical Analgesics
Contains 1 Patch
3-15/16” x 5-1/2” (10 cm x 14 cm)

CHATTEM®
A SANOFI COMPANY
Dist. by Chattem, Inc., a Sanofi Company
P.O. Box 2219
Chattanooga, TN 37409-0219 USA
©2020
www.icyhot.com Made in Japan.

Label